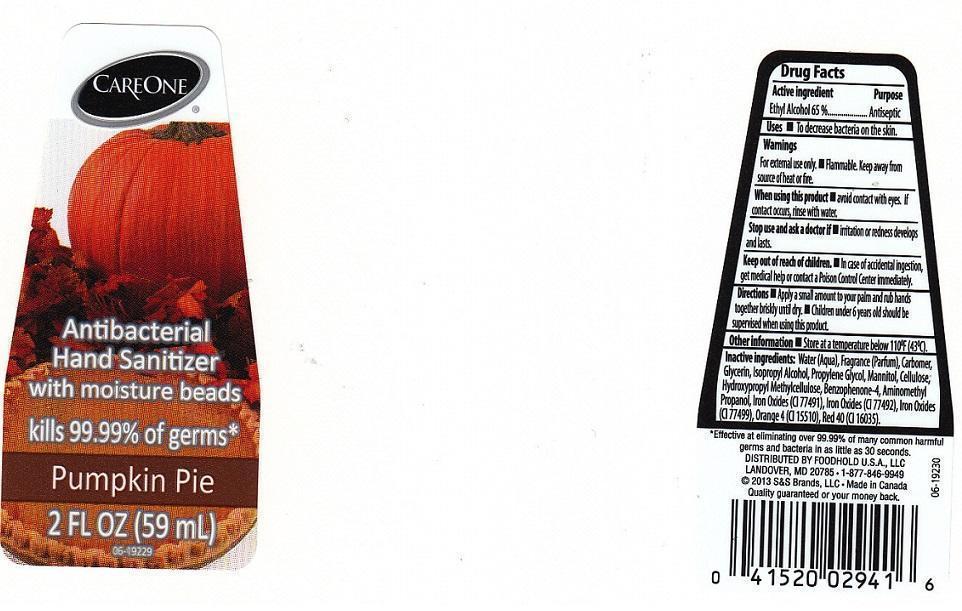 DRUG LABEL: CARE ONE
NDC: 41520-496 | Form: LIQUID
Manufacturer: AMERICAN SALES COMPANY
Category: otc | Type: HUMAN OTC DRUG LABEL
Date: 20131028

ACTIVE INGREDIENTS: ALCOHOL 650 mg/1 mL
INACTIVE INGREDIENTS: WATER; CARBOMER 934; GLYCERIN; ISOPROPYL ALCOHOL; PROPYLENE GLYCOL; MANNITOL; POWDERED CELLULOSE; HYPROMELLOSES; SULISOBENZONE; AMINOMETHYLPROPANOL; FERRIC OXIDE RED; FERRIC OXIDE YELLOW; FERROSOFERRIC OXIDE; D&C ORANGE NO. 4; FD&C RED NO. 40

DRUG FACTS

ACTIVE INGREDIENT

ETHYL ALCOHOL 65%

PURPOSE

ANTISEPTIC

USES

FOR EXTERNAL USE ONLY. FLAMMABLE. KEEP AWAY FROM SOURCE OF HEAT OR FIRE

WHEN USING THIS PRODUCT

AVOID CONTACT WITH EYES. IF CONTACT OCCURS, RINSE WITH WATER

STOP USE AND ASK A DOCTOR IF

IRRITATION OR REDNESS DEVELOPS AND LASTS

KEEP OUT OF REACH OF CHILDREN

IN CASE OF ACCIDENTAL INGESTION, GET MEDICAL HELP OR CONTACT A POISON CONTROL CENTER IMMEDIATELY

WARNINGS

FOR EXTERNAL USE ONLY. FLAMMABLE. KEEP AWAY FROM SOURCE OF HEAT OR FIRE

WHEN USING THIS PRODUCT

AVOID CONTACT WITH EYES. IF CONTACT OCCURS, RINSE WITH WATER

STOP USE AND ASK A DOCTOR IF

IRRITATION OR REDNESS DEVELOPS AND LASTS

KEEP OUT OF REACH OF CHILDREN

IN CASE OF ACCIDENTAL INGESTION, GET MEDICAL HELP OR CONTACT A POISON CONTROL CENTER IMMEDIATELY

DIRECTIONS

APPLY A SMALL AMOUNT TO YOUR PALM AND RUB HANDS TOGETHER BRISKLY UNTIL DRY. CHILDREN UNDER 6 YEARS OLD SHOULD BE SUPERVISED WHEN USING THIS PRODUCT

OTHER INFORMATION

STORE AT A TEMPERATURE BELOW 110°F (43°C)

INACTIVE INGREDIENTS

WATER (AQUA), FRAGRANCE (PARFUM), CARBOMER, GLYCERIN, ISOPROPYL ALCOHOL, PROPYLENE GLYCOL, MANNITOL, CELLULOSE, HYDROXYPROPYL METHYLCELLULOSE, BENZOPHENONE-4, AMINOMETHYL PROPANOL, IRON OXIDE (CI 77491), IRON OXIDES (CI 77492), IRON OXIDES (CI 77499), ORANGE 4 (CI 15510), RED 40 (CI 16035)